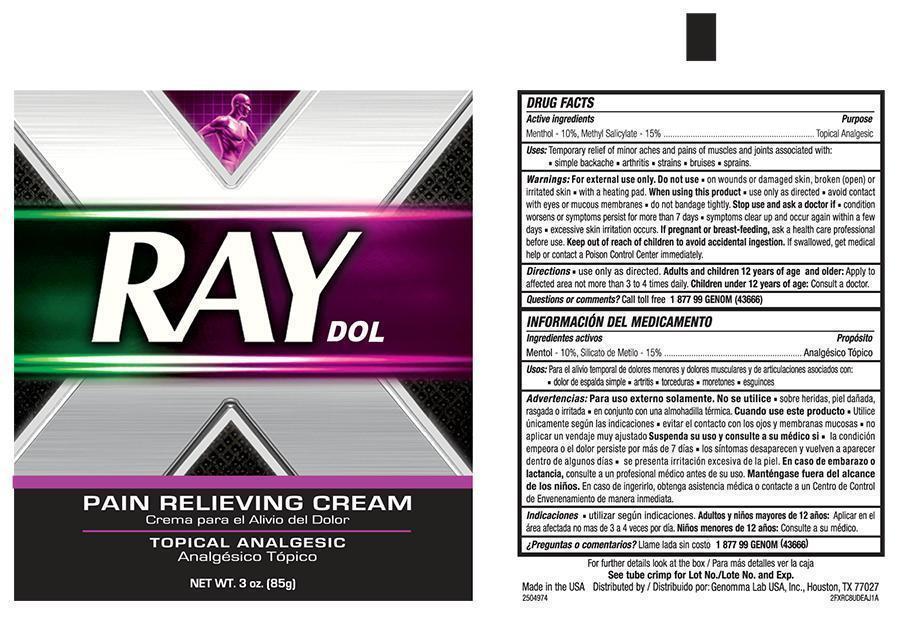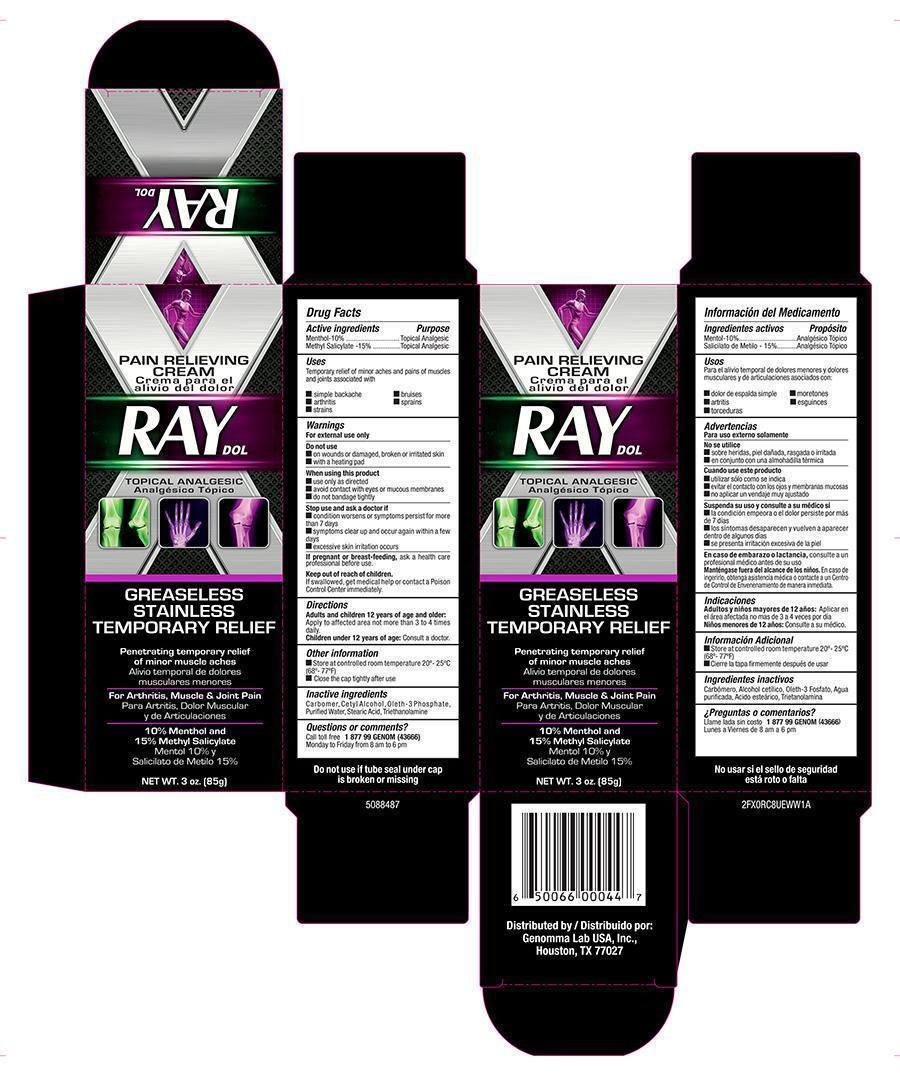 DRUG LABEL: RAY DOL
NDC: 50066-057 | Form: CREAM
Manufacturer: Genomma Lab USA Inc.
Category: otc | Type: HUMAN OTC DRUG LABEL
Date: 20140107

ACTIVE INGREDIENTS: MENTHOL 100 mg/1 g; METHYL SALICYLATE 150 mg/1 g
INACTIVE INGREDIENTS: CARBOMER 940; CETYL ALCOHOL; TROLAMINE; WATER; STEARIC ACID; OLETH-3 PHOSPHATE

Active Ingredients

Menthol - 10%

Methyl salicylate - 15%

Purpose

Topical Analgesic

Topical Analgesic

Uses

Temporary relief of minor aches and pains of muscle and joints associated with

- simple back aches
- arthritis
- strains
- bruises
- sprains

Warnings

For external use only

Do not use

- on wounds, damaged, broken or irritated skin
- with a heating pad

When using this product

- use only as directed
- avoid contact with eyes or mucous membranes
- Do not apply bandage tightly

Stop use and ask doctor if

- Condition worsens, or symtoms persist for more than 7 days
- symptoms clear up and occur again within a few days
- excessive skin irritation occurs

- If pregnant or breast feeding, ask a health professional before use.

KEEP OUT OF REACH OF CHILDREN

Keep this and all drugs out of the reach of children. If swallowed, get medical help or contact a Poison Control Center immediately.

Directions

- Adults and children 2 years of age and older; Apply to affected area not more than 3 to 4 times daily.
- Children under 2 years of age; consult a doctor.

Other information

- Store at controlled room temperature 20°- 25°C (68° to 77°F)
- Close cap tightly after use.

Inactive ingredients

Carbomer, Cetyl Alcohol, Oleth-3 Phosphate, Purified Water, Stearic acid, Triethanolamine

Principal Display Panel - 3.0 oz Carton

RAY DOL

Topical Analgesic

Greaselees Stainless

Temporary Relief

Penetrating temporary relief of minor muscle aches

For Arthritis, Muscle & Joint Pain

10% Menthol and

15% Methyl Salicylate

Net WT. 3.0 oz (85g)

Principal Display Panel - 3.0 oz Tube

RAY DOL

Pain Relieving Cream

Topical Analgesic

Net WT. 3.0 oz (85g)